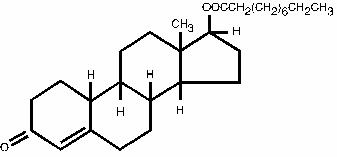 DRUG LABEL: Unknown
Manufacturer: Watson Laboratories, Inc.
Category: prescription | Type: HUMAN PRESCRIPTION DRUG LABELING
Date: 20070208
DEA Schedule: CIII

NANDROLONE DECANOATE INJECTION USP
FOR INTRAMUSCULAR USE C-III
Rx only

DESCRIPTION

A sterile oleaginous solution containing per mL: Nandrolone Decanoate 100 mg with Benzyl Alcohol 10% as solubilizer/preservative, in Sesame Oil q.s., and Nandrolone Decanoate 200 mg with Benzyl Alcohol 5% as solubilizer/preservative, in Sesame Oil q.s.

Nandrolone decanoate (C28H44O3) occurs as a fine, white to creamy white, crystalline powder. It is odorless, or may have a slight odor.

Nandrolone decanoate is soluble in chloroform, in alcohol, in acetone, and in vegetable oils. It is practically insoluble in water.

CLINICAL PHARMACOLOGY

Anabolic steroids are synthetic derivatives of testosterone. Certain clinical effects and adverse reactions demonstrate the androgenic properties of this class of drugs. Complete dissociation of anabolic and androgenic effects has not been achieved. The actions of anabolic steroids are therefore similar to those of male sex hormones with the possibility of causing serious disturbances of growth and sexual development if given to young children. Anabolic steroids suppress the gonadotropic functions of the pituitary and may exert a direct effect upon the testis.

Anabolic steroids have been reported to increase low-density lipoproteins and decrease high-density lipoproteins. These changes revert to normal on discontinuation of treatment.

INDICATIONS AND USAGE

Nandrolone decanoate is indicated for the management of the anemia of renal insufficiency and has been shown to increase hemoglobin and red cell mass. Surgically induced anephric patients have been reported to be less responsive.

CONTRAINDICATIONS

1. Male patients with carcinoma of the breast or with known or suspected carcinoma of the prostate.
2. Carcinoma of the breast in females with hypercalcemia: androgenic anabolic steroids may stimulate osteolytic resorption of bones.
3. Pregnancy, because of masculinization of the fetus.
4. Nephrosis or the nephrotic phase of nephritis.

WARNINGS

PELIOSIS HEPATIS, A CONDITION IN WHICH LIVER AND SOMETIMES SPLENIC TISSUE IS REPLACED WITH BLOOD-FILLED CYSTS, HAS BEEN REPORTED IN PATIENTS RECEIVING ANDROGENIC ANABOLIC STEROID THERAPY. THESE CYSTS ARE SOMETIMES PRESENT WITH MINIMAL HEPATIC DYSFUNCTION, BUT AT OTHER TIMES THEY HAVE BEEN ASSOCIATED WITH LIVER FAILURE. THEY ARE OFTEN NOT RECOGNIZED UNTIL LIFE-THREATENING LIVER FAILURE OR INTRA-ABDOMINAL HEMORRHAGE DEVELOPS. WITHDRAWAL OF DRUG USUALLY RESULTS IN COMPLETE DISAPPEARANCE OF LESIONS.

LIVER CELL TUMORS ARE ALSO REPORTED. MOST OFTEN THESE TUMORS ARE BENIGN AND ANDROGEN-DEPENDENT, BUT FATAL MALIGNANT TUMORS HAVE BEEN REPORTED. WITHDRAWAL OF DRUG OFTEN RESULTS IN REGRESSION OR CESSATION OF PROGRESSION OF THE TUMOR. HOWEVER, HEPATIC TUMORS ASSOCIATED WITH ANDROGENS OR ANABOLIC STEROIDS ARE MUCH MORE VASCULAR THAN OTHER HEPATIC TUMORS AND MAY BE SILENT UNTIL LIFE-THREATENING INTRA-ABDOMINAL HEMORRHAGE DEVELOPS.

BLOOD LIPID CHANGES THAT ARE KNOWN TO BE ASSOCIATED WITH INCREASED RISK OF ATHEROSCLEROSIS ARE SEEN IN PATIENTS TREATED WITH ANDROGENS AND ANABOLIC STEROIDS. THESE CHANGES INCLUDE DECREASED HIGH-DENSITY LIPOPROTEIN AND SOMETIMES INCREASED LOW-DENSITY LIPOPROTEIN. THE CHANGES MAY BE VERY MARKED AND COULD HAVE A SERIOUS IMPACT ON THE RISK OF ATHEROSCLEROSIS AND CORONARY ARTERY DISEASE.

Hypercalcemia may develop both spontaneously and as a result of androgen therapy in women with disseminated breast carcinoma. If it develops while on this agent, the drug should be discontinued. Caution is required in administering these agents to patients with cardiac, renal or hepatic disease. Cholestatic jaundice is associated with therapeutic use of anabolic and androgenic steroids. Edema may occur occasionally with or without congestive heart failure. Concomitant administration of adrenal steroids or ACTH may add to the edema.

In children, anabolic steroid treatment may accelerate bone maturation without producing compensatory gain in linear growth. This adverse effect may result in compromised adult stature. The younger the child the greater the risk of compromising final mature height. The effect on bone maturation should be monitored by assessing bone age of the wrist and hand every six months.

This drug has not been shown to be safe and effective for the enhancement of athletic performance. Because of the potential risk of serious adverse health effects, this drug should not be used for such purpose.

PRECAUTIONS

General

Women should be observed for signs of virilization (deepening of the voice, hirsutism, acne, clitorimegaly and menstrual irregularities). Discontinuation of drug therapy at the time of evidence of mild virilism is necessary to prevent irreversible virilization. Such virilization is usual following anabolic steroid use in high doses.

The insulin or oral hypoglycemic dosage may need adjustment in diabetic patients who receive anabolic steroids.

Information for patients

The physician should instruct patients to report any of the following side effects of androgenic anabolic steroids:

Hoarseness, acne, changes in menstrual periods, more hair on the face, nausea, vomiting, changes in skin color, or ankle swelling.

Laboratory tests

Women with disseminated breast carcinoma should have frequent determination of urine and serum calcium levels during the course of anabolic therapy (see WARNINGS section).

If children are treated, periodic (every six months) X-ray examinations of bone age should be made during treatment to determine the rate of bone maturation and the effects of anabolic therapy on the epiphyseal centers.

Hemoglobin and hematocrit should be checked periodically for polycythemia in patients who are receiving high doses of anabolic steroids.

Serum lipids and high-density lipoprotein cholesterol should be determined periodically.

Because of the hepatotoxicity associated with the use of 17-alpha-alkylated anabolic steroids, liver function tests should be obtained periodically.

Drug interactions

Anticoagulants. Anabolic steroids may increase sensitivity to oral anticoagulants. Dosage of the anticoagulant may have to be decreased in order to maintain the prothrombin time at the desired therapeutic level. Patients receiving oral anticoagulant therapy require close monitoring, especially when anabolic steroids are started or stopped.

Drug/laboratory test interactions

Anabolic steroid therapy may decrease thyroxine-binding globulin resulting in decreased total T4 serum levels and increased resin uptake of T3 and T4. Free thyroid hormone levels remain unchanged.

Anabolic steroids may cause an increase in prothrombin time.

Carcinogenesis, mutagenesis, impairment of fertility

Nandrolone decanoate has not been tested in laboratory animals for carcinogenic or mutagenic effects. Liver cell tumors have been reported in patients receiving androgenic anabolic steroid therapy (see WARNINGS section). Geriatric patients treated with anabolics may be at an increased risk for prostatic hypertrophy and prostatic carcinoma.

Pregnancy

Pregnancy Category X.
See CONTRAINDICATIONS section.

Nursing mothers

It is not known whether anabolic steroids are excreted in human milk. Many drugs are excreted in human milk and because of the potential for serious adverse reactions in nursing infants from anabolic steroids, a decision should be made whether to discontinue nursing or to discontinue the drug, taking into account the importance of the drug to the mother.

Pediatric use

The safety and efficacy of nandrolone decanoate in children with metastatic breast cancer (rarely found) has not been established. Anabolic agents may accelerate epiphyseal maturation more rapidly than linear growth in children, and the effect may continue for six months after the drug has been stopped. Therefore, therapy should be monitored by X-ray studies at six month intervals in order to avoid the risk of compromising the adult height.

ADVERSE REACTIONS

Hepatic:

Hepatocellular neoplasms and peliosis hepatis have been reported in association with long-term androgenic anabolic steroid therapy (see WARNINGS section).

Genitourinary System:

In men. a. Prepubertal: Phallic enlargement and increased frequency of erections. b. Postpubertal: Inhibition of testicular function, testicular atrophy and oligospermia, impotence, chronic priapism, epididymitis and bladder irritability.

In women: Clitoral enlargement, menstrual irregularities.

In both sexes: Increased or decreased libido.

CNS:

Habituation, excitation, insomnia, depression.

Gastrointestinal:

Nausea, vomiting, diarrhea.

Hematologic:

Bleeding in patients on concomitant anticoagulant therapy (see PRECAUTIONS, Drug Interactions).

Breast:

Gynecomastia.

Larynx:

Deepening of the voice in women.

Hair:

Hirsutism and male pattern of baldness in women.

Skin:

Acne (especially in women and prepubertal boys.)

Skeletal:

Premature closure of epiphyses in children (see PRECAUTIONS, Pediatric use).

Fluid and Electrolytes:

Edema, retention of serum electrolytes (sodium, chloride, potassium, phosphate, calcium).

Metabolic/Endocrine:

Decreased glucose tolerance (see PRECAUTIONS, General), increased serum levels of low-density lipoprotein and decreased levels of high-density lipoprotein (see PRECAUTIONS, Laboratory tests), increased creatine and creatinine excretion, increased serum levels of creatinine phosphokinase (CPK). Some virilizing changes in women are irreversible even after prompt discontinuance of therapy and are not prevented by concomitant use of estrogens (see PRECAUTIONS).

DRUG ABUSE AND DEPENDENCE

Nandrolone decanoate injection is classified as a Schedule III controlled substance under the Anabolic Steroids Control Act of 1990.

OVERDOSAGE

There have been no reports of acute overdosage with the anabolics.

DOSAGE AND ADMINISTRATION

Nandrolone decanoate injection is intended for deep intramuscular injection only, into the gluteal muscle preferably.

Dosage should be based on therapeutic response and consideration of the benefit to risk ratio. Duration of therapy will depend on the response of the condition and the appearance of adverse reactions. If possible, therapy should be intermittent.

Nandrolone decanoate should be regarded as adjunctive therapy and adequate quantities of nutrients should be consumed in order to obtain maximal therapeutic effects. For example, when it is used in the treatment of refractory anemia, adequate iron intake is required for a maximal response.

Anemia of Renal Disease

A dose of 50 to 100 mg per week is recommended for women and 100 to 200 mg per week for men. Drug therapy should be discontinued if no hematologic improvement is seen within the first six months. For children from 2 to 13 years of age, the average dose is 25 to 50 mg every 3 to 4 weeks.

Parenteral drug products should be inspected visually for particulate matter and discoloration prior to administration, whenever the solution and container permit.

HOW SUPPLIED

Nandrolone Decanoate Injection USP, 100 mg per mL is available in multiple dose vials of 2 mL, in cartons of 10.

Nandrolone Decanoate Injection USP, 200 mg per mL is available in single dose vials of 1 mL, in cartons of 25.

Store at 20°-25°C (68°-77°F) [See USP Controlled Room Temperature].
PROTECT FROM LIGHT. Store in carton until contents are used.
Literature revised: March 2006

Product Nos.: 0432-02, 0710-01

Watson Laboratories, Inc.

Corona, CA 92880 USA